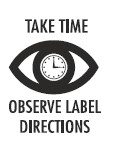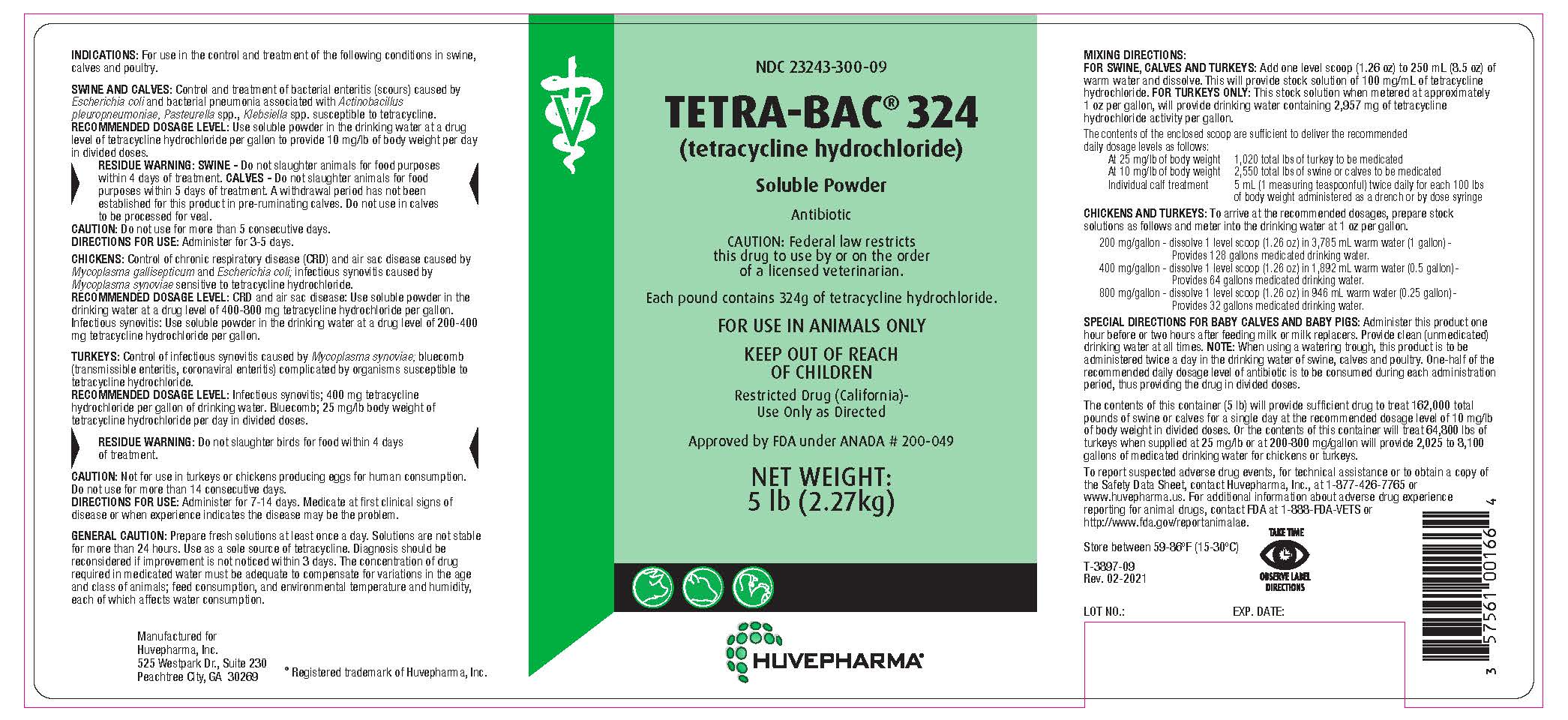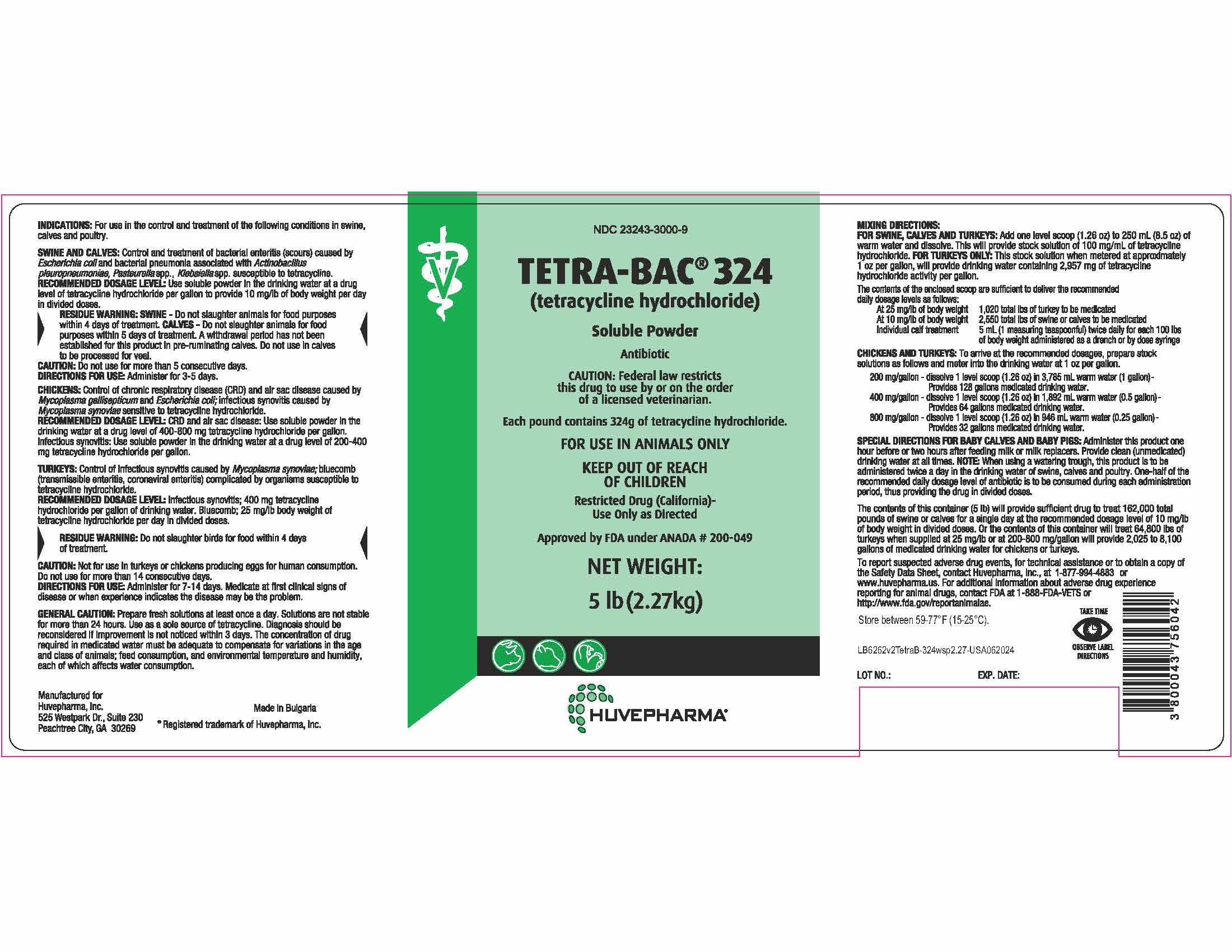 DRUG LABEL: Tetra-Bac
NDC: 23243-3000 | Form: POWDER, FOR SOLUTION
Manufacturer: Huvepharma, Inc
Category: animal | Type: PRESCRIPTION ANIMAL DRUG LABEL
Date: 20250317

ACTIVE INGREDIENTS: TETRACYCLINE HYDROCHLORIDE 324 g/453.6 g

INDICATIONS AND USAGE

NDC 23243-3000-9

TETRA-BAC® 324

(tetracycline hydrochloride)
Soluble Powder
Antibiotic

CAUTION: Federal law restricts this drug to use by or on the order of a licensed veterinarian.

Each pound contains 324g of tetracycline hydrochloride.

FOR USE IN ANIMALS ONLY

KEEP OUT OF REACH OF CHILDREN

Restricted Drug (California)-Use Only as Directed

Approved by FDA under ANADA # 200-049

NET WEIGHT:
5 lb (2.27g)

INDICATIONS AND USAGE

INDICATIONS: For use in the control and treatment of the following conditions in swine, calves and poultry.

SWINE AND CALVES: Control and treatment of bacterial enteritis (scours) caused by Escherichia coli and bacterial pneumonia associated with Actinobacillus pleuropneumoniae, Pasteurella spp., Klebsiella spp. susceptible to tetracycline.

RECOMMENDED DOSAGE LEVEL: Use soluble powder in the drinking water at a drug level of tetracycline hydrochloride per gallon to provide 10 mg/lb of body weight per day in divided doses.

RESIDUE WARNING

RESIDUE WARNING: SWINE- Do not slaughter animals for food purposes within 4 days of treatment. CALVES- Do not slaughter animals for food purposes within 5 days of treatment. A withdrawal period has not been established for this product in pre-ruminating calves. Do not use in calves to be processed for veal.

PRECAUTIONS

CAUTION: Do not use for more than 5 consecutive days.
DIRECTIONS FOR USE: Administer for 3-5 days.

INDICATIONS AND USAGE

CHICKENS: Control of chronic respiratory disease (CRD) and air sac disease caused by Mycoplasma gallisepticum and Escherichia coli; infectious synovitis caused by Mycoplasma synoviae sensitive to tetracycline hydrochloride.

RECOMMENDED DOSAGE LEVEL: CRD and air sac disease: Use soluble powder in the drinking water at a drug level of 400-800 mg tetracycline hydrochloride per gallon. Infectious synovitis: Use soluble powder in the drinking water at a drug level of 200-400 mg tetracycline hydrochloride per gallon.

INDICATIONS AND USAGE

TURKEYS: Control of infectious synovitis caused by Mycoplasma synoviae; bluecomb (transmissible enteritis, coronaviral enteritis) complicated by organisms susceptible to tetracycline hydrochloride.
RECOMMENDED DOSAGE LEVEL: Infectious synovitis; 400 mg tetracycline hydrochloride per gallon of drinking water. Bluecomb; 25 mg/lb body weight of tetracycline hydrochloride per day in divided doses.

RESIDUE WARNING

RESIDUE WARNING: Do not slaughter birds for food within 4 days of treatment.

PRECAUTIONS

CAUTION: Not for use in turkeys or chickens producing eggs for human consumption. Do not use for more than 14 consecutive days.
DIRECTIONS FOR USE: Administer for 7-14 days. Medicate at first clinical signs of disease or when experience indicates the disease may be the problem.

GENERAL PRECAUTIONS

GENERAL CAUTION: Prepare fresh solutions at least once a day. Solutions are not stable
for more than 24 hours. Use as a sole source of tetracycline. Diagnosis should be
reconsidered if improvement is not noticed within 3 days. The concentration of drug
required in medicated water must be adequate to compensate for variations in the age
and class of animals; feed consumption, and environmental temperature and humidity,
each of which affects water consumption.

Manufactured for

Huvepharma, Inc. Made in Bulgaria
525 Westpark Dr., Suite 230
Peachtree City, GA 30269 ® Registered trademark of Huvepharma, Inc.

DOSAGE AND ADMINISTRATION

MIXING DIRECTIONS:
FOR SWINE, CALVES AND TURKEYS: Add one level scoop (1.26 oz) to 250 mL (8.5 oz) of
warm water and dissolve. This will provide stock solution of 100 mg/mL of tetracycline
hydrochloride. FOR TURKEYS ONLY: This stock solution when metered at approximately
1 oz per gallon, will provide drinking water containing 2,957 mg of tetracycline
hydrochloride activity per gallon.

The contents of the enclosed scoop are sufficient to deliver the recommended
daily dosage levels as follows:

At 25 mg/lb of body weight 1,020 total lbs of turkey to be medicated

At 10 mg/lb of body weight 2,550 total lbs of swine or calves to be medicated

Individual calf treatment 5 mL (1 measuring teaspoon) twice daily for each 100 lbs
of body weight administered as a drench or by dose syringe

CHICKENS AND TURKEYS: To arrive at the recommended dosages, prepare stock
solutions as follows and meter into the drinking water at 1 oz per gallon.

200 mg/gallon - dissolve 1 level scoop (1.26 oz) in 3,785 mL warm water (1 gallon)-
Provides 128 gallons medicated drinking water.
400 mg/gallon - dissolve 1 level scoop (1.26 oz) in 1,892 mL warm water (0.5 gallon)-
Provides 64 gallons medicated drinking water.
800 mg/gallon - dissolve 1 level scoop (1.26 oz) in 946 mL warm water (0.25 gallon)-
Provides 32 gallons medicated drinking water.

SPECIAL DIRECTIONS FOR BABY CALVES AND BABY PIGS: Administer this product one
hour before or two hours after feeding milk or milk replacers. Provide clean (unmedicated)
drinking water at all times. NOTE: When using a watering trough, this product is to be
administered twice a day in the drinking water of swine, calves and poultry. One-half of the
recommended daily dosage level of antibiotic is to be consumed during each administration
period, thus providing the drug in divided doses.

The contents of this container (5 lb) will provide sufficient drug to treat 162,000 total
pounds of swine or calves for a single day at the recommended dosage level of 10 mg/lb
of body weight in divided doses. Or the contents of this container will treat 64,800 lbs of
turkeys when supplied at 25 mg/lb or at 200-800 mg/gallon will provide 2,025 to 8,100
gallons of medicated drinking water for chickens or turkeys.

To report suspected adverse drug events, for technical assistance or to obtain a copy of
the Safety Data Sheet, contact Huvepharma, Inc., at 1-877-994-4883 or
www.huvepharma.us. For additional information about adverse drug experience
reporting for animal drugs, contact FDA at 1-888-FDA-VETS or
http://www.fda.gov/reportanimalae.

STORAGE AND HANDLING

Store between 59-77ºF (15-25ºC)

LB6262v2TetraB-324wsp2.27-USA062024

LOT NO.: EXP. DATE: